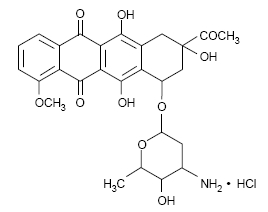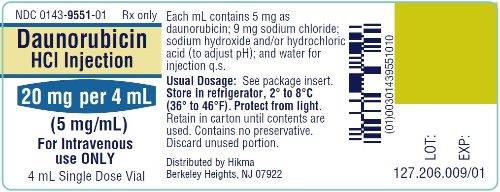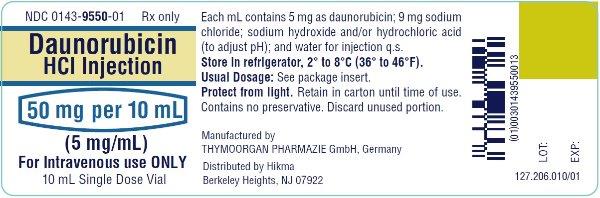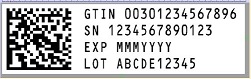 DRUG LABEL: Daunorubicin Hydrochloride
NDC: 0143-9551 | Form: INJECTION
Manufacturer: Hikma Pharmaceuticals USA Inc.
Category: prescription | Type: HUMAN PRESCRIPTION DRUG LABEL
Date: 20240215

ACTIVE INGREDIENTS: DAUNORUBICIN HYDROCHLORIDE 5 mg/1 mL
INACTIVE INGREDIENTS: SODIUM CHLORIDE 9 mg/1 mL; WATER

DAUNORUBICIN HYDROCHLORIDE INJECTION

Rx ONLY

WARNINGS

- 1.Daunorubicin Hydrochloride Injection must be given into a rapidly flowing intravenous infusion. It must never be given by the intramuscular or subcutaneous route. Severe local tissue necrosis will occur if there is extravasation during administration.
- 2.Myocardial toxicity manifested in its most severe form by potentially fatal congestive heart failure may occur either during therapy or months to years after termination of therapy. The incidence of myocardial toxicity increases after a total cumulative dose exceeding 400 to 550 mg/m^2 in adults, 300 mg/m^2 in children more than 2 years of age, or 10 mg/kg in children less than 2 years of age.
- 3.Severe myelosuppression occurs when used in therapeutic doses; this may lead to infection or hemorrhage.
- 4.It is recommended that daunorubicin hydrochloride be administered only by physicians who are experienced in leukemia chemotherapy and in facilities with laboratory and supportive resources adequate to monitor drug tolerance and protect and maintain a patient compromised by drug toxicity. The physician and institution must be capable of responding rapidly and completely to severe hemorrhagic conditions and/or overwhelming infection.
- 5.Dosage should be reduced in patients with impaired hepatic or renal function.

DESCRIPTION

Daunorubicin hydrochloride is the hydrochloride salt of an anthracycline cytotoxic antibiotic produced by a strain of Streptomyces coeruleorubidus. It is provided as a deep red sterile liquid in vials for intravenous administration only. Each mL contains 5 mg daunorubicin (equivalent to 5.34 mg of daunorubicin hydrochloride), 9 mg sodium chloride; sodium hydroxide and/or hydrochloric acid (to adjust pH), and water for injection, q.s. It has the following structural formula which may be described with the chemical name of (1S,3S)-3-Acetyl-1,2,3,4,6,11-hexahydro-3,5,12-trihydroxy-10-methoxy-6,11-dioxo-1-naphthacenyl 3-amino-2,3,6-trideoxy-α-L-lyxo-hexopyranoside hydrochloride. Its molecular formula is C27H29NO10•HCl with a molecular weight of 563.99. It is a hygroscopic crystalline powder. The pH of a 5 mg/mL aqueous solution is 4 to 5.

CLINICAL PHARMACOLOGY

Mechanism of Action

Daunorubicin has antimitotic and cytotoxic activity through a number of proposed mechanisms of action. Daunorubicin forms complexes with DNA by intercalation between base pairs. It inhibits topoisomerase II activity by stabilizing the DNA-topoisomerase II complex, preventing the religation portion of the ligation-religation reaction that topoisomerase II catalyzes. Single strand and double strand DNA breaks result.

Daunorubicin hydrochloride may also inhibit polymerase activity, affect regulation of gene expression, and produce free radical damage to DNA.

Daunorubicin hydrochloride possesses an antitumor effect against a wide spectrum of animal tumors, either grafted or spontaneous.

Pharmacokinetics

General

Following intravenous injection of Daunorubicin hydrochloride, plasma levels of daunorubicin decline rapidly, indicating rapid tissue uptake and concentration. Thereafter, plasma levels decline slowly with a half-life of 45 minutes in the initial phase and 18.5 hours in the terminal phase. By 1 hour after drug administration, the predominant plasma species is daunorubicinol, an active metabolite, which disappears with a half-life of 26.7 hours.

Distribution

Daunorubicin hydrochloride is rapidly and widely distributed in tissues, with highest levels in the spleen, kidneys, liver, lungs, and heart. The drug binds to many cellular components, particularly nucleic acids. There is no evidence that daunorubicin crosses the blood-brain barrier, but the drug apparently crosses the placenta.

Metabolism and Elimination

Daunorubicin hydrochloride is extensively metabolized in the liver and other tissues, mainly by cytoplasmic aldo-keto reductases, producing daunorubicinol, the major metabolite which has antineoplastic activity. Approximately 40% of the drug in the plasma is present as daunorubicinol within 30 minutes and 60% in 4 hours after a dose of daunorubicin. Further metabolism via reduction cleavage of the glycosidic bond, 4-O demethylation, and conjugation with both sulfate and glucuronide have been demonstrated. Simple glycosidic cleavage of daunorubicin or daunorubicinol is not a significant metabolic pathway in man. Twenty-five percent of an administered dose of daunorubicin hydrochloride is eliminated in an active form by urinary excretion and an estimated 40% by biliary excretion.

Special Populations

Pediatric Patients

Although appropriate studies with daunorubicin hydrochloride have not been performed in the pediatric population, cardiotoxicity may be more frequent and occur at lower cumulative doses in children.

Geriatric Patients

Although appropriate studies with daunorubicin hydrochloride have not been performed in the geriatric population, cardiotoxicity may be more frequent in the elderly. Caution should also be used in patients who have inadequate bone marrow reserves due to old age. In addition, elderly patients are more likely to have age-related renal function impairment, which may require reduction of dosage in patients receiving daunorubicin hydrochloride.

Renal and Hepatic Impairment

Doses of daunorubicin hydrochloride should be reduced in patients with hepatic and renal impairment. Patients with serum bilirubin concentrations of 1.2 to 3 mg/dL should receive 75% of the usual daily dose and patients with serum bilirubin concentrations greater than 3 mg/dL should receive 50% of the usual daily dose. Patients with serum creatinine concentrations of greater than 3 mg/dL should receive 50% of the usual daily dose. (See WARNINGS, Evaluation of Hepatic and Renal Function).

Clinical Studies

In the treatment of adult acute nonlymphocytic leukemia, daunorubicin hydrochloride, used as a single agent, has produced complete remission rates of 40 to 50%, and in combination with cytarabine, has produced complete remission rates of 53 to 65%.

The addition of daunorubicin hydrochloride to the two-drug induction regimen of vincristine-prednisone in the treatment of childhood acute lymphocytic leukemia does not increase the rate of complete remission. In children receiving identical CNS prophylaxis and maintenance therapy (without consolidation), there is prolongation of complete remission duration (statistically significant, p<0.02) in those children induced with the three drug (daunorubicin-vincristine-prednisone) regimen as compared to two drugs. There is no evidence of any impact of daunorubicin hydrochloride on the duration of complete remission when a consolidation (intensification) phase is employed as part of a total treatment program.

In adult acute lymphocytic leukemia, in contrast to childhood acute lymphocytic leukemia, daunorubicin hydrochloride during induction significantly increases the rate of complete remission, but not remission duration, compared to that obtained with vincristine, prednisone, and L-asparaginase alone. The use of daunorubicin hydrochloride in combination with vincristine, prednisone, and L-asparaginase has produced complete remission rates of 83% in contrast to a 47% remission in patients not receiving daunorubicin hydrochloride.

INDICATIONS AND USAGE

Daunorubicin hydrochloride in combination with other approved anticancer drugs is indicated for remission induction in acute nonlymphocytic leukemia (myelogenous, monocytic, erythroid) of adults and for remission induction in acute lymphocytic leukemia of children and adults.

CONTRAINDICATIONS

Daunorubicin hydrochloride is contraindicated in patients who have shown a hypersensitivity to it.

WARNINGS

Bone Marrow

Daunorubicin hydrochloride is a potent bone marrow suppressant. Suppression will occur in all patients given a therapeutic dose of this drug. Therapy with daunorubicin hydrochloride should not be started in patients with pre-existing drug-induced bone marrow suppression unless the benefit from such treatment warrants the risk. Persistent, severe myelosuppression may result in superinfection or hemorrhage.

Cardiac Effects

Special attention must be given to the potential cardiac toxicity of daunorubicin hydrochloride, particularly in infants and children. Pre-existing heart disease and previous therapy with doxorubicin are co-factors of increased risk of daunorubicin-induced cardiac toxicity and the benefit-to-risk ratio of daunorubicin hydrochloride therapy in such patients should be weighed before starting daunorubicin hydrochloride. In adults, at total cumulative doses less than 550 mg/m^2, acute congestive heart failure is seldom encountered. However, rare instances of pericarditis-myocarditis, not dose-related, have been reported.

In adults, at cumulative doses exceeding 550 mg/m^2, there is an increased incidence of drug-induced congestive heart failure. Based on prior clinical experience with doxorubicin, this limit appears lower, namely 400 mg/m^2, in patients who received radiation therapy that encompassed the heart.

In infants and children, there appears to be a greater susceptibility to anthracycline-induced cardiotoxicity compared to that in adults, which is more clearly dose-related. Anthracycline therapy (including daunorubicin) in pediatric patients has been reported to produce impaired left ventricular systolic performance, reduced contractility, congestive heart failure or death. These conditions may occur months to years following cessation of chemotherapy. This appears to be dose-dependent and aggravated by thoracic irradiation. Long-term periodic evaluation of cardiac function in such patients should, thus, be performed. In both children and adults, the total dose of daunorubicin hydrochloride administered should also take into account any previous or concomitant therapy with other potentially cardiotoxic agents or related compounds such as doxorubicin.

There is no absolutely reliable method of predicting the patients in whom acute congestive heart failure will develop as a result of the cardiac toxic effect of daunorubicin hydrochloride. However, certain changes in the electrocardiogram and a decrease in the systolic ejection fraction from pre-treatment baseline may help to recognize those patients at greatest risk to develop congestive heart failure. On the basis of the electrocardiogram, a decrease equal to or greater than 30% in limb lead QRS voltage has been associated with a significant risk of drug-induced cardiomyopathy. Therefore, an electrocardiogram and/or determination of systolic ejection fraction should be performed before each course of daunorubicin hydrochloride. In the event that one or the other of these predictive parameters should occur, the benefit of continued therapy must be weighed against the risk of producing cardiac damage.

Early clinical diagnosis of drug-induced congestive heart failure appears to be essential for successful treatment.

Evaluation of Hepatic and Renal Function

Significant hepatic or renal impairment can enhance the toxicity of the recommended doses of daunorubicin hydrochloride; therefore, prior to administration, evaluation of hepatic function and renal function using conventional clinical laboratory tests is recommended (see DOSAGE AND ADMINISTRATION section).

Pregnancy

Daunorubicin hydrochloride may cause fetal harm when administered to a pregnant woman. An increased incidence of fetal abnormalities (parieto-occipital cranioschisis, umbilical hernias, or rachischisis) and abortions was reported in rabbits at doses of 0.05 mg/kg/day or approximately 1/100th of the highest recommended human dose on a body surface area basis. Rats showed an increased incidence of esophageal, cardiovascular and urogenital abnormalities as well as rib fusions at doses of 4 mg/kg/day or approximately 1/2 the human dose on a body surface area basis. Decreases in fetal birth weight and post-delivery growth rate were observed in mice. There are no adequate and well-controlled studies in pregnant women. If this drug is used during pregnancy, or if the patient becomes pregnant while taking this drug, the patient should be apprised of the potential hazard to the fetus. Women of childbearing potential should be advised to avoid becoming pregnant.

Secondary Leukemias

There have been reports of secondary leukemias in patients exposed to topoisomerase II inhibitors when used in combination with other antineoplastic agents or radiation therapy.

Extravasation at Injection Site

Extravasation of daunorubicin hydrochloride at the site of intravenous administration can cause severe local tissue necrosis. (See ADVERSE REACTIONS section)

PRECAUTIONS

General

Therapy with daunorubicin hydrochloride requires close patient observation and frequent complete blood-count determinations. Cardiac, renal, and hepatic function should be evaluated prior to each course of treatment.

Appropriate measures must be taken to control any systemic infection before beginning therapy with daunorubicin hydrochloride.

Daunorubicin hydrochloride may transiently impart a red coloration to the urine after administration, and patients should be advised to expect this.

Laboratory Tests

Daunorubicin hydrochloride may induce hyperuricemia secondary to rapid lysis of leukemic cells. As a precaution, allopurinol administration is usually begun prior to initiating antileukemic therapy. Blood uric acid levels should be monitored and appropriate therapy initiated in the event that hyperuricemia develops.

Carcinogenesis, Mutagenesis, Impairment of Fertility

Daunorubicin hydrochloride, when injected subcutaneously into mice, causes fibrosarcomas to develop at the injection site. When administered to mice thrice weekly intraperitoneally, no carcinogenic effect was noted after 18 months of observation. In male rats administered daunorubicin thrice weekly for 6 months, at 1/70th the recommended human dose on a body surface area basis, peritoneal sarcomas were found at 18 months. A single IV dose of daunorubicin administered to rats at 1.6 fold the recommended human dose on a body surface area basis caused mammary adenocarcinomas to appear at 1 year. Daunorubicin was mutagenic in vitro (Ames assay, V79 hamster cell assay), and clastogenic in vitro (CCRFCEM human lymphoblasts) and in vivo (SCE assay in mouse bone marrow) tests.

In male dogs at a daily dose of 0.25 mg/kg administered intravenously, testicular atrophy was noted at autopsy. Histologic examination revealed total aplasia of the spermatocyte series in the seminiferous tubules with complete aspermatogenesis.

Pregnancy Category D

(See WARNINGS section)

Nursing Mothers

It is not known whether this drug is excreted in human milk. Because many drugs are excreted in human milk and because of the potential for serious adverse reactions in nursing infants from daunorubicin, mothers should be advised to discontinue nursing during daunorubicin therapy.

Elderly

See CLINICAL PHARMACOLOGY, Special Populations, Geriatric Patients section.

Pediatric Use

See CLINICAL PHARMACOLOGY, Special Populations, Pediatric Patients section and WARNINGS, Cardiac Effects section.

Drug Interactions

Use of daunorubicin in a patient who has previously received doxorubicin increases the risk of cardiotoxicity. Daunorubicin hydrochloride should not be used in patients who have previously received the recommended maximum cumulative doses of doxorubicin or daunorubicin hydrochloride. Cyclophosphamide used concurrently with daunorubicin hydrochloride may also result in increased cardiotoxicity.

Dosage reduction of daunorubicin hydrochloride may be required when used concurrently with other myelosuppressive agents.

Hepatotoxic medications, such as high-dose methotrexate, may impair liver function and increase the risk of toxicity.

ADVERSE REACTIONS

Dose-limiting toxicity includes myelosuppression and cardiotoxicity (see WARNINGS section). Other reactions include:

Cutaneous

Reversible alopecia occurs in most patients. Rash, contact dermatitis and urticaria have occurred rarely.

Gastrointestinal

Acute nausea and vomiting occur but are usually mild. Antiemetic therapy may be of some help. Mucositis may occur 3 to 7 days after administration. Diarrhea and abdominal pain have occasionally been reported.

Local

If extravasation occurs during administration, severe local tissue necrosis, severe cellulitis, thrombophlebitis, or painful induration can result.

Acute Reactions

Rarely, anaphylactoid reaction, fever, and chills can occur. Hyperuricemia may occur, especially in patients with leukemia, and serum uric acid levels should be monitored.

DOSAGE AND ADMINISTRATION

Parenteral drug products should be inspected visually for particulate matter prior to administration, whenever solution and container permit.

Principles

In order to eradicate the leukemic cells and induce a complete remission, a profound suppression of the bone marrow is usually required. Evaluation of both the peripheral blood and bone marrow is mandatory in the formulation of appropriate treatment plans.

It is recommended that the dosage of daunorubicin hydrochloride be reduced in instances of hepatic or renal impairment. For example, using serum bilirubin and serum creatinine as indicators of liver and kidney function, the following dose modifications are recommended:

Serum Bilirubin | Serum Creatinine | Dose Reduction
1.2 to 3 mg% | — | 25%
>3 mg% | — | 50%
— | >3 mg% | 50%

Representative Dose Schedules and Combination for the Approved Indication of Remission Induction in Adult Acute Nonlymphocytic Leukemia

In Combination

For patients under age 60, daunorubicin hydrochloride 45 mg/m^2/day IV on days 1, 2, and 3 of the first course and on days 1, 2 of subsequent courses AND cytosine arabinoside 100 mg/m^2/day IV infusion daily for 7 days for the first course and for 5 days for subsequent courses.

For patients 60 years of age and above, daunorubicin hydrochloride 30 mg/m^2/day IV on days 1, 2, and 3 of the first course and on days 1, 2 of subsequent courses AND cytosine arabinoside 100 mg/m^2/day IV infusion daily for 7 days for the first course and for 5 days for subsequent courses. This daunorubicin hydrochloride dose-reduction is based on a single study and may not be appropriate if optimal supportive care is available.

The attainment of a normal-appearing bone marrow may require up to three courses of induction therapy. Evaluation of the bone marrow following recovery from the previous course of induction therapy determines whether a further course of induction treatment is required.

Representative Dose Schedule and Combination for the Approved Indication of Remission Induction in Pediatric Acute Lymphocytic Leukemia

In Combination

Daunorubicin hydrochloride 25 mg/m^2 IV on day 1 every week, vincristine 1.5 mg/m^2 IV on day 1 every week, prednisone 40 mg/m^2 PO daily. Generally, a complete remission will be obtained within four such courses of therapy; however, if after four courses the patient is in partial remission, an additional one or, if necessary, two courses may be given in an effort to obtain a complete remission.

In children less than 2 years of age or below 0.5 m^2 body surface area, it has been recommended that the daunorubicin hydrochloride dosage calculation should be based on weight (1 mg/kg) instead of body surface area.

Representative Dose Schedules and Combination for the Approved Indication of Remission Induction in Adult Acute Lymphocytic Leukemia

In Combination

Daunorubicin hydrochloride 45 mg/m^2/day IV on days 1, 2, and 3 AND vincristine 2 mg IV on days 1, 8, and 15; prednisone 40 mg/m^2/day PO on days 1 through 22, then tapered between days 22 to 29; L-asparaginase 500 IU/kg/day x 10 days IV on days 22 through 32.

The sterile vial contents provide 20 mg of daunorubicin, with 5 mg of daunorubicin per mL. The desired dose is withdrawn into a syringe containing 10 mL to 15 mL of 0.9% Sodium Chloride Injection, USP and then injected into the tubing or sidearm in a rapidly flowing IV infusion of 5% Dextrose Injection, USP or 0.9% Sodium Chloride Injection, USP. Daunorubicin hydrochloride should not be administered mixed with other drugs or heparin.

Storage and Handling

Store unopened vials in refrigerator, 2° to 8°C (36° to 46°F). Store prepared solution for infusion at room temperature, 15° to 30°C (59° to 86°F) for up to 24 hours. Contains no preservative. Discard unused portion. Protect from light.

If daunorubicin hydrochloride contacts the skin or mucosae, the area should be washed thoroughly with soap and water. Procedures for proper handling and disposal of anticancer drugs should be considered. Several guidelines on this subject have been published.^1-7 There is no general agreement that all of the procedures recommended in the guidelines are necessary or appropriate.

HOW SUPPLIED

Daunorubicin Hydrochloride Injection, 5 mg/mL, is available as a deep red sterile liquid in butyl-rubber-stoppered vials as follows:

NDC 0143-9551-10 20 mg, 4 mL per vial, single-use vials; carton of 10.

NDC 0143-9550-01 50 mg, 10 mL per vial, single-use vial; individually-boxed.

To report SUSPECTED ADVERSE REACTIONS, contact Hikma Pharmaceuticals USA Inc. at 1-877-845-0689, or the FDA at 1-800-FDA-1088 or www.fda.gov/medwatch.

For Product Inquiry call 1-877-845-0689.

REFERENCES

- 1.Recommendations for the Safe Handling of Parenteral Antineoplastic Drugs. NIH Publication No. 83-2621. For sale by the Superintendent of Documents, U.S. Government Printing Office, Washington, D.C. 20402.
- 2.AMA Council Report. Guidelines for Handling Parenteral Antineoplastics. JAMA, March 15,1985.
- 3.National Study Commission on Cytotoxic Exposure—Recommendations for Handling Cytotoxic Agents. Available from Louis R Jeffrey, Sc.D., Chairman, National Study Commission on Cytotoxic Exposure, Massachusetts College of Pharmacy and Allied Health Sciences, 179 Longwood Avenue, Boston, Massachusetts 02115.
- 4.Clinical Oncological Society of Australia: Guidelines and recommendations for safe handling of antineoplastic agents. Med J Australia 1:426-428, 1983.
- 5.Jones RB, et al: Safe handling of chemotherapeutic agents: A report from the Mount Sinai Medical Center, Ca—A Cancer Journal for Clinicians Sept/Oct, 258-263, 1983.
- 6.American Society of Hospital Pharmacists technical assistance bulletin on handling cytotoxic and hazardous drugs. Am J Hosp Pharm 47:1033-1049, 1990.
- 7.OSHA Work Practice Guidelines for Personnel Dealing with Cytotoxic (Antineoplastic) Drugs. Am J Hosp Pharm 43:1193-1204, 1986.

Manufactured by:
THYMOORGAN PHARMAZIE GmbH,
Schiffgraben 23, 38690 Goslar, Germany

Distributed by:
Hikma Pharmaceuticals USA Inc.
Berkeley Heights, NJ 07922
Revised March 2020

127.207.005/01

VIAL LABEL 20 mg/4 mL

NDC 0143-9551-01 Rx only
Daunorubicin
HCl Injection
20 mg per 4 mL
(5 mg/mL)
For Intravenous
use ONLY
4 mL Single Dose Vial

VIAL LABEL 50 mg/10 mL

NDC 0143-9550-01 Rx only
Daunorubicin
HCl Injection
50 mg per 10 mL
(5 mg/mL)
For Intravenous use ONLY
10 mL Single Dose Vial

SERIALIZATION IMAGE

Representative Carton Serialization Image